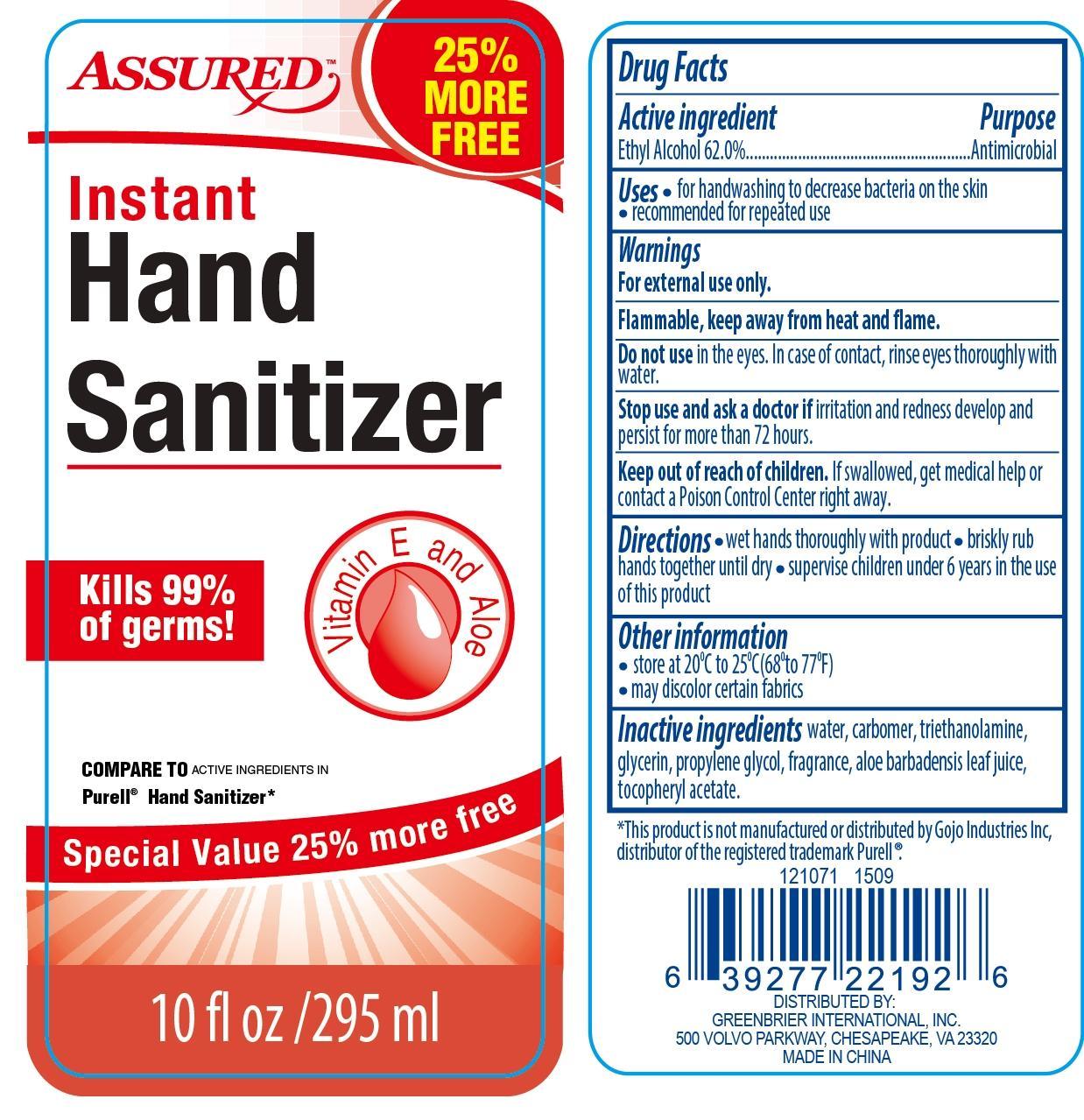 DRUG LABEL: Assured Instant
NDC: 58503-082 | Form: GEL
Manufacturer: China Ningbo Shangge Cosmetic Technology Corp.
Category: otc | Type: HUMAN OTC DRUG LABEL
Date: 20190913

ACTIVE INGREDIENTS: ALCOHOL 62 g/100 g
INACTIVE INGREDIENTS: WATER; CARBOMER COPOLYMER TYPE A; TROLAMINE; GLYCERIN; PROPYLENE GLYCOL; ALOE VERA LEAF; .ALPHA.-TOCOPHEROL ACETATE

Assured Instant

Active Ingredient Purpose

Ethyl Alcohol 62.0% ..................... Antimicrobial

Uses

- for handwashing to decrease bacteria on the skin
- recommended for repeated use

Keep out of reach of children. If swallowed, get medical help or contact a Poison Control Center right away.

INDICATIONS AND USAGE

Assured

Instant Hand Sanitizer

Kills 99% of germs!

Vitamin E and Aloe

Compare to Active Ingredients in Purell® Hand Sanitizer*

Special Value 25% more free

10 fl oz / 295 ml

*This product is not manufactured or distributed by Gojo Industries Inc, distributor of the registered trademark Purell®

Directions

- wet hands thoroughly with product
- briskly rub hands together until dry
- supervise children under 6 years in the use of this product

Warnings

For external use only.

Flammable, keep away from heat and flame.

Do not use in the eyes. In case of contact, rinse eyes thoroughly with water.

Stop use and ask a doctor if irritation and redness develop and persist for more than 72 hours.

Inactive Ingredients

water, carbomer, triethanolamine, glycerin, propylene glycol, fragrance, aloe barbadensis leaf juice, tocopheryl acetate.